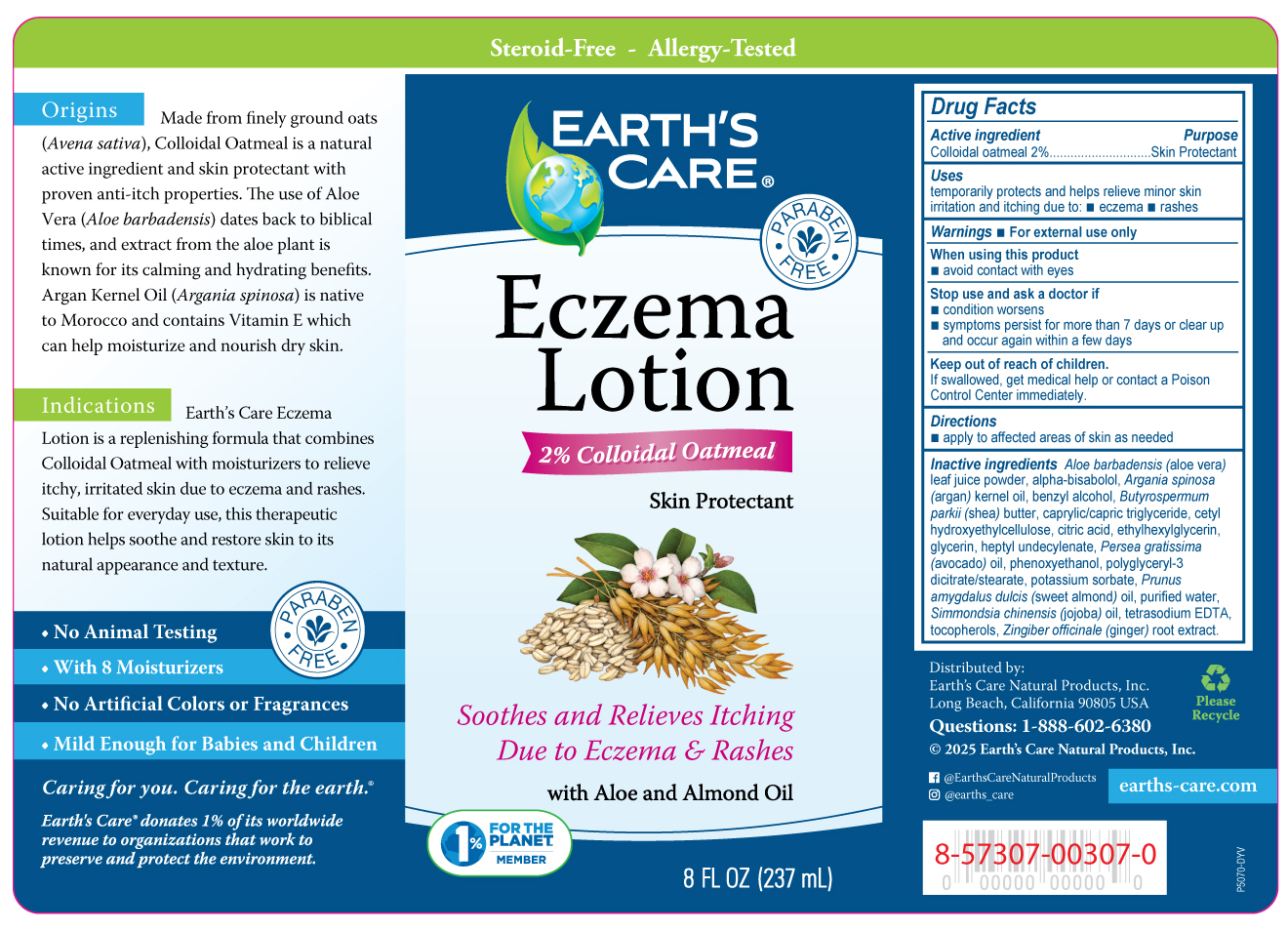 DRUG LABEL: Earths Care Eczema
NDC: 24286-1571 | Form: LOTION
Manufacturer: DLC Laboratories, Inc.
Category: otc | Type: HUMAN OTC DRUG LABEL
Date: 20251208

ACTIVE INGREDIENTS: OATMEAL 1.8 g/100 mL
INACTIVE INGREDIENTS: POLYGLYCERYL-3 DICITRATE/STEARATE; CAPRYLIC/CAPRIC TRIGLYCERIDE; WATER; GINGER OIL; ALOE VERA LEAF; CETYL HYDROXYETHYLCELLULOSE (350000 MW); EDETATE SODIUM; GLYCERIN; SHEA BUTTER; ALMOND OIL; HEPTYL UNDECYLENATE; JOJOBA OIL; AVOCADO OIL; .ALPHA.-BISABOLOL, (+/-)-; ARGAN OIL; TOCOPHEROL; POTASSIUM SORBATE; PHENOXYETHANOL; ETHYLHEXYLGLYCERIN; BENZYL ALCOHOL; ANHYDROUS CITRIC ACID

Earth's Care® Eczema

Drug Facts

Active ingredient

Colloidal oatmeal 2%

Purpose

Skin Protectant

Uses

temporarily protects and helps relieve minor skin irritation and itching due to:

- eczema
- rashes

Warnings

- For external use only

When using this product

- avoid contact with eyes

Stop use and ask a doctor if

- condition worsens
- symptoms persist for more than 7 days or clear up and occur again within a few days

Keep out of reach of children.

If swallowed, get medical help or contact a Poison Control Center immediately.

Directions

- apply to affected areas of skin as needed

Inactive ingredients

Aloe barbadensis (aloe vera) extract, alpha-bisabolol, Argania spinosa (argan) kernel oil, benzyl alcohol, Butyrospermum parkii (shea) butter, caprylic/capric triglyceride, cetyl hydroxyethylcellulose, citric acid, ethylhexylglycerin, glycerin, heptyl undecylenate, Persea gratissima (avocado) oil, phenoxyethanol, polyglyceryl-3 dicitrate/stearate, potassium sorbate, Prunus amygdalus dulcis (sweet almond) oil, purified water, Simmondsia chinensis (jojoba) oil, tetrasodium EDTA, tocopherols, Zingiber officinale (ginger) root extract.

Questions

1-888-602-6380

Distributed by:
Earth's Care Natural Products, Inc.
Long Beach, California 90805 USA

PRINCIPAL DISPLAY PANEL - 237 mL Bottle Label

Steroid-Free-Allergy Tested

EARTH'S
CARE®

• PARABEN
FREE •

Eczema
Lotion

2% Colloidal Oatmeal

Skin Protectant

Soothes and Relieves Itching

Due to Eczema & Rashes

with Aloe and Almond Oil

1%
FOR THE
PLANETSM
MEMBER

8 FL OZ (237 mL)